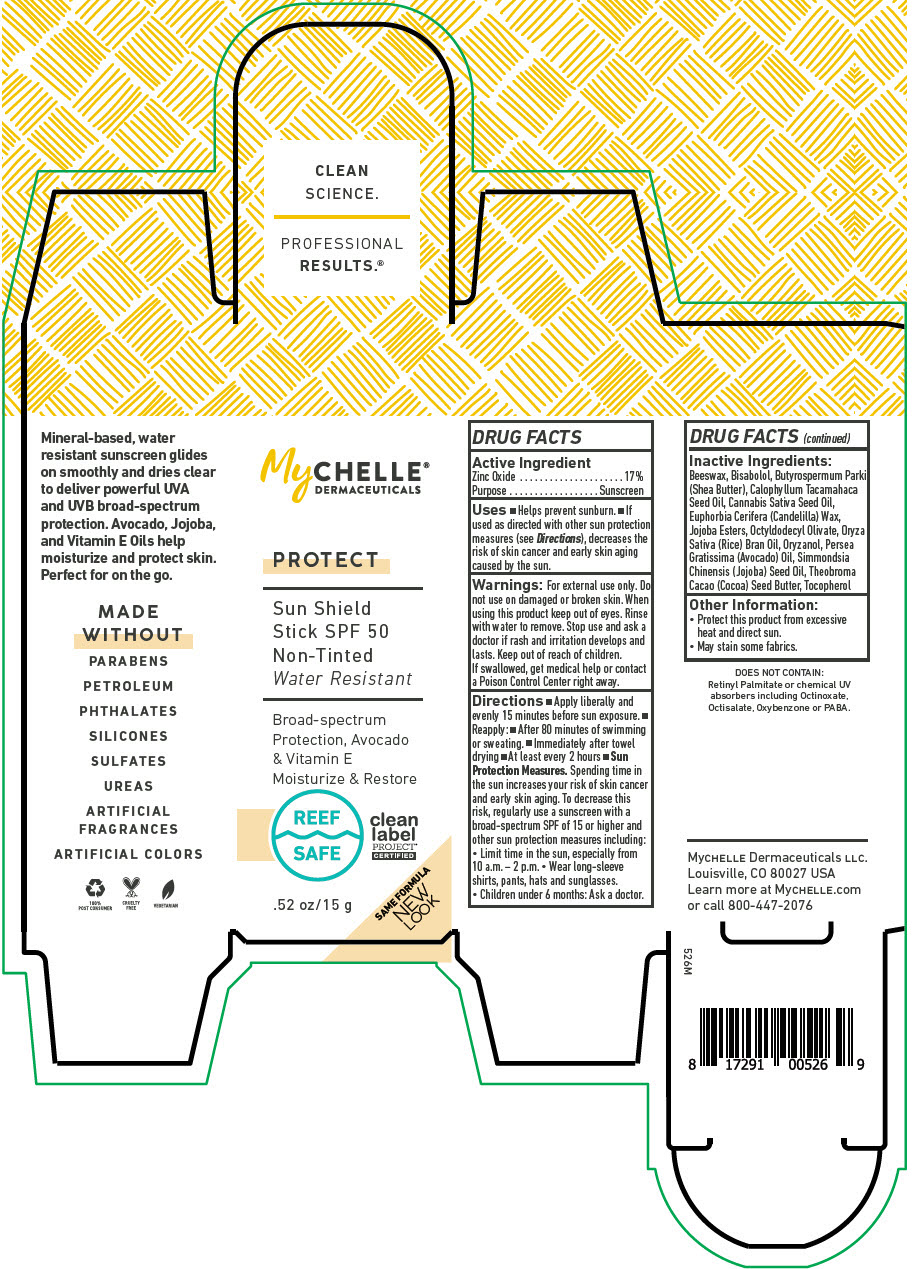 DRUG LABEL: MyChelle Dermaceuticals Sun Shield SPF 50 Non-Tinted 
NDC: 72805-101 | Form: STICK
Manufacturer: French Transit, Ltd.
Category: otc | Type: HUMAN OTC DRUG LABEL
Date: 20220107

ACTIVE INGREDIENTS: Zinc Oxide 17 g/100 g
INACTIVE INGREDIENTS: YELLOW WAX; LEVOMENOL; SHEA BUTTER; Calophyllum Tacamahaca Seed Oil; Cannabis Sativa Seed Oil; CANDELILLA WAX; HYDROGENATED JOJOBA OIL, RANDOMIZED; RICE BRAN OIL; Oryzanol; AVOCADO OIL; JOJOBA OIL; COCOA BUTTER; Tocopherol

MyChelle® Dermaceuticals Sun Shield Stick SPF 50 Non-Tinted

DRUG FACTS

Active Ingredient

Zinc Oxide 17%

Purpose

Sunscreen

Uses

- Helps prevent sunburn.
- If used as directed with other sun protection measures (see Directions), decreases the risk of skin cancer and early skin aging caused by the sun.

Warnings

For external use only. Do not use on damaged or broken skin. When using this product keep out of eyes. Rinse with water to remove. Stop use and ask a doctor if rash and irritation develops and lasts.

Keep out of reach of children. If swallowed, get medical help or contact a Poison Control Center right away.

Directions

- Apply liberally and evenly 15 minutes before sun exposure.
- Reapply:
  - After 80 minutes of swimming or sweating.
  - Immediately after towel drying
  - At least every 2 hours
- Sun Protection Measures. Spending time in the sun increases your risk of skin cancer and early skin aging. To decrease this risk, regularly use a sunscreen with a broad-spectrum SPF of 15 or higher and other sun protection measures including:
  - Limit time in the sun, especially from 10 a.m. – 2 p.m.
  - Wear long-sleeve shirts, pants, hats and sunglasses.
  - Children under 6 months: Ask a doctor.

Inactive Ingredients

Beeswax, Bisabolol, Butyrospermum Parkii (Shea Butter), Calophyllum Tacamahaca Seed Oil, Cannabis Sativa Seed Oil, Euphorbia Cerifera (Candelilla) Wax, Jojoba Esters, Octyldodecyl Olivate, Oryza Sativa (Rice) Bran Oil, Oryzanol, Persea Gratissima (Avocado) Oil, Simmondsia Chinensis (Jojoba) Seed Oil, Theobroma Cacao (Cocoa) Seed Butter, Tocopherol

Other Information

- Protect this product from excessive heat and direct sun.
- May stain some fabrics.

PRINCIPAL DISPLAY PANEL - 15 g Container Box

MyCHELLE®
DERMACEUTICALS

PROTECT

Sun Shield
Stick SPF 50
Non-Tinted

Water Resistant

Broad-spectrum
Protection, Avocado
& Vitamin E
Moisturize & Restore

REEF
SAFE

clean
label
PROJECT®
CERTIFIED

.52 oz/15 g

SAME FORMULA
NEW
LOOK